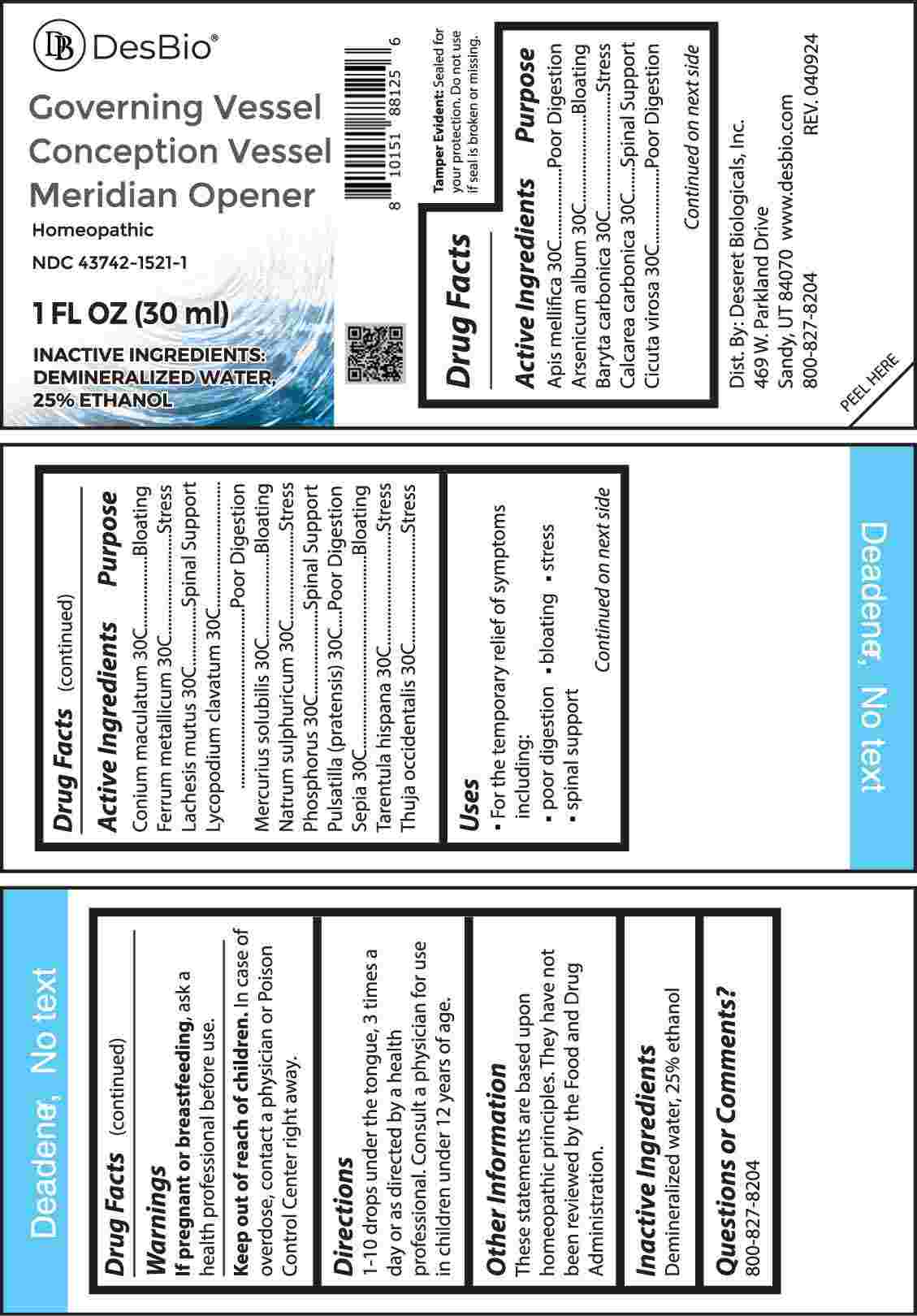 DRUG LABEL: Governing Vessel Conception Vessel Meridian Opener
NDC: 43742-1521 | Form: LIQUID
Manufacturer: Deseret Biologicals, Inc.
Category: homeopathic | Type: HUMAN OTC DRUG LABEL
Date: 20240416

ACTIVE INGREDIENTS: APIS MELLIFERA 30 [hp_C]/1 mL; ARSENIC TRIOXIDE 30 [hp_C]/1 mL; BARIUM CARBONATE 30 [hp_C]/1 mL; OYSTER SHELL CALCIUM CARBONATE, CRUDE 30 [hp_C]/1 mL; CICUTA VIROSA ROOT 30 [hp_C]/1 mL; CONIUM MACULATUM FLOWERING TOP 30 [hp_C]/1 mL; IRON 30 [hp_C]/1 mL; LACHESIS MUTA VENOM 30 [hp_C]/1 mL; LYCOPODIUM CLAVATUM SPORE 30 [hp_C]/1 mL; MERCURIUS SOLUBILIS 30 [hp_C]/1 mL; SODIUM SULFATE 30 [hp_C]/1 mL; PHOSPHORUS 30 [hp_C]/1 mL; PULSATILLA PRATENSIS WHOLE 30 [hp_C]/1 mL; SEPIA OFFICINALIS JUICE 30 [hp_C]/1 mL; LYCOSA TARANTULA 30 [hp_C]/1 mL; THUJA OCCIDENTALIS LEAFY TWIG 30 [hp_C]/1 mL
INACTIVE INGREDIENTS: WATER; ALCOHOL

DRUG FACTS:

ACTIVE INGREDIENTS:

Apis Mellifica 30C, Arsenicum Album 30C, Baryta Carbonica 30C, Calcarea Carbonica 30C, Cicuta Virosa 30C, Conium Maculatum 30C, Ferrum Metallicum 30C, Lachesis Mutus 30C, Lycopodium Clavatum 30C, Mercurius Solubilis 30C, Natrum Sulphuricum 30C, Phosphorus 30C, Pulsatilla (Pratensis) 30C, Sepia 30C, Tarentula Hispana 30C, Thuja Occidentalis 30C.

PURPOSE:

Apis Mellifica – Poor Digestion, Arsenicum Album - Bloating, Baryta Carbonica - Stress, Calcarea Carbonica – Spinal Support, Cicuta Virosa – Poor Digestion, Conium Maculatum - Bloating, Ferrum Metallicum - Stress, Lachesis Mutus – Spinal Support, Lycopodium Clavatum – Poor Digestion, Mercurius Solubilis - Bloating, Natrum Sulphuricum - Stress, Phosphorus – Spinal Support, Pulsatilla (Pratensis) – Poor Digestion, Sepia - Bloating, Tarentula Hispana - Stress, Thuja Occidentalis - Stress

USES:

• For the temporary relief of symptoms including:

• poor digestion • bloating • stress • spinal support

WARNINGS:

If pregnant or breast-feeding, ask a health professional before use.

Keep out of reach of children. In case of overdose, contact a physician or Poison Control Center right away.

Tamper Evident: Sealed for your protection. Do not use if seal is broken or missing.

KEEP OUT OF REACH OF CHILDREN:

In case of overdose, contact a physician or Poison Control Center right away.

DIRECTIONS:

1-10 drops under the tongue, 3 times a day or as directed by a health professional. Consult a physician for use in children under 12 years of age.

INACTIVE INGREDIENTS:

Demineralized water, 25% ethanol

QUESTIONS:

Dist. By: Deseret Biologicals, Inc.

469 W. Parkland Drive

Sandy, UT 84070

www.desbio.com

800-827-8204

PACKAGE LABEL DISPLAY:

Des Bio

Governing Vessel

Conception Vessel

Meridian Opener

Homeopathic

NDC 43742-1521-1

1 FL OZ (30 ml)